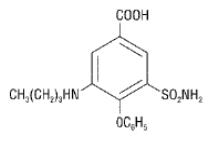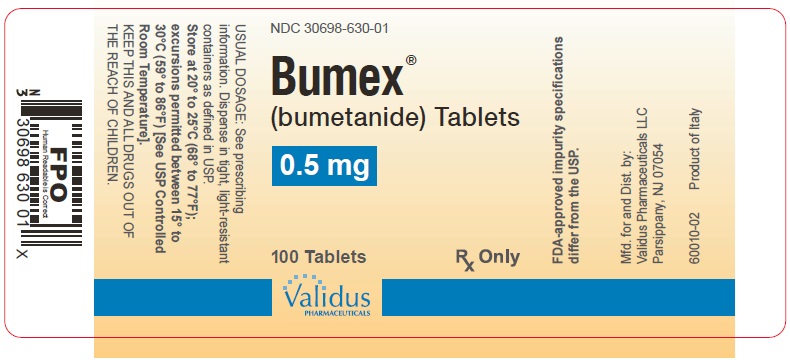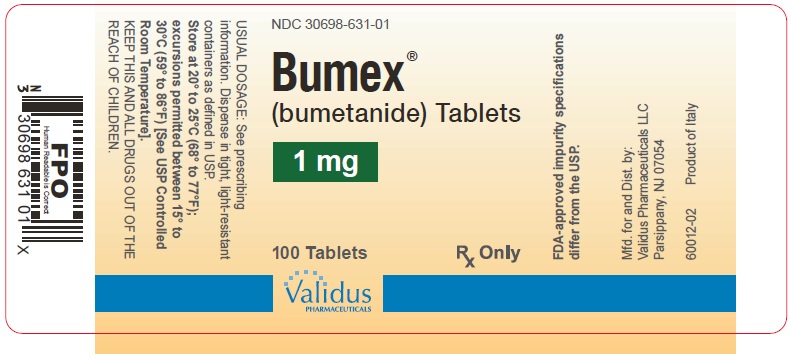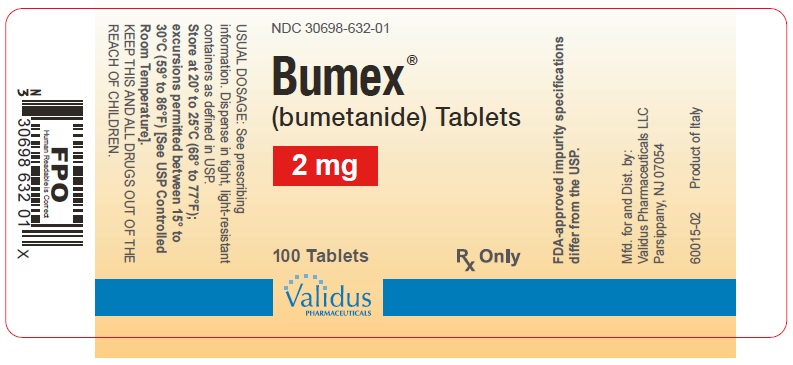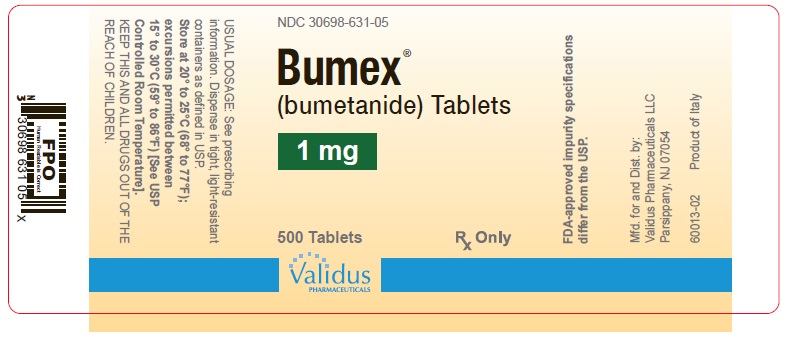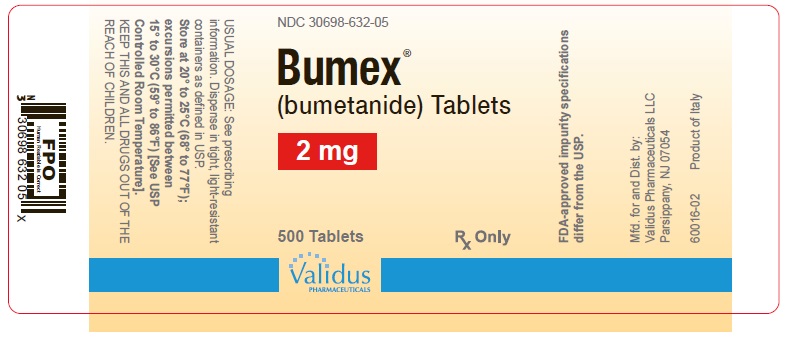 DRUG LABEL: Bumex
NDC: 30698-630 | Form: TABLET
Manufacturer: Validus Pharmaceuticals LLC
Category: prescription | Type: HUMAN PRESCRIPTION DRUG LABEL
Date: 20250908

ACTIVE INGREDIENTS: BUMETANIDE 0.5 mg/1 1
INACTIVE INGREDIENTS: ANHYDROUS LACTOSE; MAGNESIUM STEARATE; MICROCRYSTALLINE CELLULOSE; STARCH, CORN; TALC; D&C YELLOW NO. 10; FD&C BLUE NO. 1

Bumex

BUMEX®
Brand of
bumetanide
TABLETS

For oral use

Rx Only

WARNING

Bumex®(bumetanide) is a potent diuretic which, if given in excessive amounts, can lead to a profound diuresis with water and electrolyte depletion. Therefore, careful medical supervision is required, and dose and dosage schedule have to be adjusted to the individual patient's needs (see DOSAGE AND ADMINISTRATION) .

DESCRIPTION

Bumex®(bumetanide) is a loop diuretic available as 0.5 mg (light green), 1 mg (yellow) and 2 mg (peach) tablets for oral administration; each tablet also contains anhydrous lactose, magnesium stearate, microcrystalline cellulose, pregelatinized starch and talc, with the following dye systems: 0.5 mg—D&C Yellow No. 10 aluminum lake and FD&C Blue No. 1 aluminum lake; 1 mg—D&C Yellow No. 10 aluminum lake; 2 mg—red iron oxide.

Chemically, bumetanide is 3-(butylamino)-4-phenoxy-5-sulfamoylbenzoic acid. It is a practically white powder having a calculated molecular weight of 364.42, and the following structural formula:

FDA-approved impurity specifications differ from the USP.

CLINICAL PHARMACOLOGY

Bumex is a loop diuretic with a rapid onset and short duration of action. Pharmacological and clinical studies have shown that 1 mg Bumex has a diuretic potency equivalent to approximately 40 mg furosemide. The major site of Bumex action is the ascending limb of the loop of Henle.

The mode of action has been determined through various clearance studies in both humans and experimental animals. Bumex inhibits sodium reabsorption in the ascending limb of the loop of Henle, as shown by marked reduction of free-water clearance (CH2O) during hydration and tubular free-water reabsorption (TCH2O) during hydropenia. Reabsorption of chloride in the ascending limb is also blocked by Bumex, and Bumex is somewhat more chloruretic than natriuretic.

Potassium excretion is also increased by Bumex, in a dose-related fashion.

Bumex may have an additional action in the proximal tubule. Since phosphate reabsorption takes place largely in the proximal tubule, phosphaturia during Bumex induced diuresis is indicative of this additional action. This is further supported by the reduction in the renal clearance of Bumex by probenecid, associated with diminution in the natriuretic response. This proximal tubular activity does not seem to be related to an inhibition of carbonic anhydrase. Bumex does not appear to have a noticeable action on the distal tubule.

Bumex decreases uric acid excretion and increases serum uric acid. Following oral administration of Bumex the onset of diuresis occurs in 30 to 60 minutes. Peak activity is reached between 1 and 2 hours. At usual doses (1 mg to 2 mg) diuresis is largely complete within 4 hours; with higher doses, the diuretic action lasts for 4 to 6 hours. Diuresis starts within minutes following an intravenous injection and reaches maximum levels within 15 to 30 minutes.

Several pharmacokinetic studies have shown that bumetanide, administered orally or parenterally, is eliminated rapidly in humans, with a half-life of between 1 and 1½ hours. Plasma protein-binding is in the range of 94% to 96%.

Oral administration of carbon-14 labeled Bumex to human volunteers revealed that 81% of the administered radioactivity was excreted in the urine, 45% of it as unchanged drug. Urinary and biliary metabolites identified in this study were formed by oxidation of the N-butyl side chain. Biliary excretion of Bumex amounted to only 2% of the administered dose.

Pediatric Pharmacology

Elimination of bumetanide appears to be considerably slower in neonatal patients compared with adults, possibly because of immature renal and hepatobiliary function in this population. Small pharmacokinetic studies of intravenous bumetanide in preterm and full-term neonates with respiratory disorders have reported an apparent half-life of approximately 6 hours, with a range up to 15 hours and a serum clearance ranging from 0.2 mL/min/kg to 1.1 mL/min/kg. In a population of neonates receiving bumetanide for volume overload, mean serum clearance rates were 2.2 mL/min/kg in patients less than 2 months of age and 3.8 mL/min/kg in patients aged 2 to 6 months. Mean serum half-life of bumetanide was 2.5 hours and 1.5 hours in patients aged less than 2 months and those aged 2 to 6 months, respectively. Elimination half-life decreased considerably during the first month of life, from a mean of approximately 6 hours at birth to approximately 2.4 hours at 1 month of age.

In preterm neonates, mean serum concentrations following a single 0.05 mg/kg dose ranged from 126 μg/L at 1 hour to 57 μg/L at 8 hours. In another study, mean serum concentrations following a single 0.05 mg/kg dose were 338 ng/mL at 30 minutes and 176 ng/mL after 4 hours. A single dose of 0.1 mg/kg produced mean serum levels of 314 ng/mL at 1 hour, and 195 ng/mL at 6 hours. Mean volume of distribution in neonates and infants has been reported to range from 0.26 L/kg to 0.39 L/kg.

The degree of protein binding of bumetanide in cord sera from healthy neonates was approximately 97%, suggesting the potential for bilirubin displacement. A study using pooled sera from critically ill neonates found that bumetanide at concentrations of 0.5 μg/mL to 50 μg/mL, but not 0.25 μg/mL, caused a linear increase in unbound bilirubin concentrations.

In 56 infants aged 4 days to 6 months, bumetanide doses ranging from 0.005 mg/kg to 0.1 mg/kg were studied for pharmacodynamic effect. Peak bumetanide excretion rates increased linearly with increasing doses of drug. Maximal diuretic effect was observed at a bumetanide excretion rate of about 7 μg/kg/h, corresponding to doses of 0.035 mg/kg to 0.040 mg/kg. Higher doses produced a higher bumetanide excretion rate but no increase in diuretic effect. Urine flow rate peaked during the first hour after drug administration in 80% of patients and by 3 hours in all patients.

Geriatric Pharmacology

In a group of ten geriatric subjects between the ages of 65 and 73 years, total bumetanide clearance was significantly lower (1.8 ± 0.3 mL/min·kg) compared with younger subjects (2.9 ± 0.2 mL/min·kg) after a single oral bumetanide 0.5 mg dose. Maximum plasma concentrations were higher in geriatric subjects (16.9 ± 1.8 ng/mL) compared with younger subjects (10.3 ± 1.5 ng/mL). Urine flow rate and total excretion of sodium and potassium were increased less in the geriatric subjects compared with younger subjects, although potassium excretion and fractional sodium excretion were similar between the two age groups. Nonrenal clearance, bioavailability, and volume of distribution were not significantly different between the two groups.

INDICATIONS AND USAGE

Bumex tablets are indicated for the treatment of edema associated with congestive heart failure, hepatic and renal disease, including the nephrotic syndrome.

Almost equal diuretic response occurs after oral and parenteral administration of bumetanide. Therefore, if impaired gastrointestinal absorption is suspected or oral administration is not practical, bumetanide should be given by the intramuscular or intravenous route.

Successful treatment with Bumex tablets following instances of allergic reactions to furosemide suggests a lack of cross-sensitivity.

CONTRAINDICATIONS

Bumex is contraindicated in anuria. Although Bumex can be used to induce diuresis in renal insufficiency, any marked increase in blood urea nitrogen or creatinine, or the development of oliguria during therapy of patients with progressive renal disease, is an indication for discontinuation of treatment with Bumex. Bumex is also contraindicated in patients in hepatic coma or in states of severe electrolyte depletion until the condition is improved or corrected. Bumex is contraindicated in patients hypersensitive to this drug.

WARNINGS

Volume and Electrolyte Depletion

The dose of Bumex should be adjusted to the patient's need. Excessive doses or too frequent administration can lead to profound water loss, electrolyte depletion, dehydration, reduction in blood volume and circulatory collapse with the possibility of vascular thrombosis and embolism, particularly in elderly patients.

Hypokalemia

Hypokalemia can occur as a consequence of Bumex administration. Prevention of hypokalemia requires particular attention in the following conditions: patients receiving digitalis and diuretics for congestive heart failure, hepatic cirrhosis and ascites, states of aldosterone excess with normal renal function, potassium-losing nephropathy, certain diarrheal states, or other states where hypokalemia is thought to represent particular added risks to the patient, i.e., history of ventricular arrhythmias.

In patients with hepatic cirrhosis and ascites, sudden alterations of electrolyte balance may precipitate hepatic encephalopathy and coma. Treatment in such patients is best initiated in the hospital with small doses and careful monitoring of the patient's clinical status and electrolyte balance. Supplemental potassium and/or spironolactone may prevent hypokalemia and metabolic alkalosis in these patients.

Ototoxicity

In cats, dogs and guinea pigs, bumetanide has been shown to produce ototoxicity. In these test animals bumetanide was 5 to 6 times more potent than furosemide and, since the diuretic potency of bumetanide is about 40 to 60 times furosemide, it is anticipated that blood levels necessary to produce ototoxicity will rarely be achieved. The potential exists, however, and must be considered a risk of intravenous therapy, especially at high doses, repeated frequently in the face of renal excretory function impairment. Potentiation of aminoglycoside ototoxicity has not been tested for bumetanide. Like other members of this class of diuretics, bumetanide probably shares this risk.

Allergy to Sulfonamides

Patients allergic to sulfonamides may show hypersensitivity to Bumex.

Thrombocytopenia

Since there have been rare spontaneous reports of thrombocytopenia from postmarketing experience, patients should be observed regularly for possible occurrence of thrombocytopenia.

PRECAUTIONS

General

Serum potassium should be measured periodically and potassium supplements or potassium sparing diuretics added if necessary. Periodic determinations of other electrolytes are advised in patients treated with high doses or for prolonged periods, particularly in those on low-salt diets.

Hyperuricemia may occur; it has been asymptomatic in cases reported to date. Reversible elevations of the BUN and creatinine may also occur, especially in association with dehydration and particularly in patients with renal insufficiency. Bumex may increase urinary calcium excretion with resultant hypocalcemia.

Diuretics have been shown to increase the urinary excretion of magnesium; this may result in hypomagnesemia.

Laboratory Tests

Studies in normal subjects receiving Bumex revealed no adverse effects on glucose tolerance, plasma insulin, glucagon and growth hormone levels, but the possibility of an effect on glucose metabolism exists. Periodic determinations of blood sugar should be done, particularly in patients with diabetes or suspected latent diabetes.

Patients under treatment should be observed regularly for possible occurrence of blood dyscrasias, liver damage or idiosyncratic reactions, which have been reported occasionally in foreign marketing experience. The relationship of these occurrences to Bumex use is not certain.

Drug Interactions

Drugs with Ototoxic Potential (see WARNINGS)

Especially in the presence of impaired renal function, the use of parenterally administered bumetanide in patients to whom aminoglycoside antibiotics are also being given should be avoided, except in life-threatening conditions.

Drugs with Nephrotoxic Potential

There has been no experience with the concurrent use of Bumex with drugs known to have a nephrotoxic potential. Therefore, the simultaneous administration of these drugs should be avoided.

Lithium

Lithium should generally not be given with diuretics (such as Bumex) because they reduce its renal clearance and add a high risk of lithium toxicity.

Probenecid

Pretreatment with probenecid reduces both the natriuresis and hyperreninemia produced by Bumex. This antagonistic effect of probenecid on Bumex natriuresis is not due to a direct action on sodium excretion but is probably secondary to its inhibitory effect on renal tubular secretion of bumetanide. Thus, probenecid should not be administered concurrently with Bumex.

Indomethacin

Indomethacin blunts the increases in urine volume and sodium excretion seen during Bumex treatment and inhibits the bumetanide-induced increase in plasma renin activity. Concurrent therapy with Bumex is thus not recommended.

Antihypertensives

Bumex may potentiate the effect of various antihypertensive drugs, necessitating a reduction in the dosage of these drugs.

Digoxin

Interaction studies in humans have shown no effect on digoxin blood levels.

Anticoagulants

Interaction studies in humans have shown Bumex to have no effect on warfarin metabolism or on plasma prothrombin activity.

Carcinogenesis, Mutagenesis and Impairment of Fertility

Bumex was devoid of mutagenic activity in various strains of Salmonella typhimurium when tested in the presence or absence of an in vitrometabolic activation system. An 18-month study showed an increase in mammary adenomas of questionable significance in female rats receiving oral doses of 60 mg/kg/day (2000 times a 2-mg human dose). A repeat study at the same doses failed to duplicate this finding.

Reproduction studies were performed to evaluate general reproductive performance and fertility in rats at oral dose levels of 10, 30, 60 or 100 mg/kg/day. The pregnancy rate was slightly decreased in the treated animals; however, the differences were small and not statistically significant.

Pregnancy

Teratogenic Effects

Bumex is neither teratogenic nor embryocidal in mice when given in doses up to 3400 times the maximum human therapeutic dose.

Bumex has been shown to be nonteratogenic, but it has a slight embryocidal effect in rats when given in doses of 3400 times the maximum human therapeutic dose and in rabbits at doses of 3.4 times the maximum human therapeutic dose. In one study, moderate growth retardation and increased incidence of delayed ossification of sternebrae were observed in rats at oral doses of 100 mg/kg/day, 3400 times the maximum human therapeutic dose. These effects were associated with maternal weight reductions noted during dosing. No such adverse effects were observed at 30 mg/kg/day (1000 times the maximum human therapeutic dose). No fetotoxicity was observed at 1000 to 2000 times the human therapeutic dose.

In rabbits, a dose-related decrease in litter size and an increase in resorption rate were noted at oral doses of 0.1 mg/kg/day and 0.3 mg/kg/day (3.4 and 10 times the maximum human therapeutic dose). A slightly increased incidence of delayed ossification of sternebrae occurred at 0.3 mg/kg/day; however, no such adverse effects were observed at the dose of 0.03 mg/kg/day. The sensitivity of the rabbit to Bumex parallels the marked pharmacologic and toxicologic effects of the drug in this species.

Bumex was not teratogenic in the hamster at an oral dose of 0.5 mg/kg/day (17 times the maximum human therapeutic dose). Bumetanide was not teratogenic when given intravenously to mice and rats at doses up to 140 times the maximum human therapeutic dose.

There are no adequate and well-controlled studies in pregnant women. A small investigational experience in the and marketing experience in other countries to date have not indicated any evidence of adverse effects on the fetus, but these data do not rule out the possibility of harmful effects. Bumex should be given to a pregnant woman only if the potential benefit justifies the potential risk to the fetus.

Nursing Mothers

It is not known whether this drug is excreted in human milk. As a general rule, nursing should not be undertaken while the patient is on Bumex since it may be excreted in human milk.

Pediatric Use

Safety and effectiveness in pediatric patients below the age of 18 have not been established.

In vitrostudies using pooled sera from critically ill neonates have shown bumetanide to be a potent displacer of bilirubin (see CLINICAL PHARMACOLOGY: Pediatric Pharmacology) . The administration of bumetanide could present a particular concern if given to critically ill or jaundiced neonates at risk for kernicterus.

Geriatric Use

Clinical studies of Bumex did not include sufficient numbers of subjects aged 65 and over to determine whether they responded differently from younger subjects. Other reported clinical experience has not identified differences in responses between the elderly and younger patients. In general, dose selection for an elderly patient should be cautious, usually starting at the low end of the dosing range, reflecting the greater frequency of decreased hepatic, renal or cardiac function, and of concomitant disease or other drug therapy.

This drug is known to be substantially excreted by the kidney, and the risk of toxic reactions to this drug may be greater in patients with impaired renal function. Because elderly patients are more likely to have decreased renal function, care should be taken in dose selection, and it may be useful to monitor renal function.

ADVERSE REACTIONS

The most frequent clinical adverse reactions considered probably or possibly related to Bumex are muscle cramps (seen in 1.1% of treated patients), dizziness (1.1%), hypotension (0.8%), headache (0.6%), nausea (0.6%) and encephalopathy (in patients with pre-existing liver disease) (0.6%). One or more of these adverse reactions have been reported in approximately 4.1% of patients treated with Bumex.

Serious skin reactions (i.e., Stevens-Johnson syndrome, toxic epidermal necrolysis) have been reported in association with bumetanide use.

Less frequent clinical adverse reactions to Bumex are impaired hearing (0.5%), pruritus (0.4%), electrocardiogram changes (0.4%), weakness (0.2%), hives (0.2%), abdominal pain (0.2%), arthritic pain (0.2%), musculoskeletal pain (0.2%), rash (0.2%) and vomiting (0.2%). One or more of these adverse reactions have been reported in approximately 2.9% of patients treated with Bumex.

Other clinical adverse reactions, which have each occurred in approximately 0.1% of patients, are vertigo, chest pain, ear discomfort, fatigue, dehydration, sweating, hyperventilation, dry mouth, upset stomach, renal failure, asterixis, itching, nipple tenderness, diarrhea, premature ejaculation and difficulty maintaining an erection.

Laboratory abnormalities reported have included hyperuricemia (in 18.4% of patients tested), hypochloremia (14.9%), hypokalemia (14.7%), azotemia (10.6%), hyponatremia (9.2%), increased serum creatinine (7.4%), hyperglycemia (6.6%), and variations in phosphorus (4.5%), CO content (4.3%), bicarbonate (3.1%) and calcium (2.4%). Although manifestations of the pharmacologic action of Bumex, these conditions may become more pronounced by intensive therapy.

Also reported have been thrombocytopenia (0.2%) and deviations in hemoglobin (0.8%), prothrombin time (0.8%), hematocrit (0.6%), WBC (0.3%) and differential counts (0.1%). There have been rare spontaneous reports of thrombocytopenia from postmarketing experience.

Diuresis induced by Bumex may also rarely be accompanied by changes in LDH (1.0%), total serum bilirubin (0.8%), serum proteins (0.7%), SGOT (0.6%), SGPT (0.5%), alkaline phosphatase (0.4%), cholesterol (0.4%) and creatinine clearance (0.3%). Increases in urinary glucose (0.7%) and urinary protein (0.3%) have also been seen.

To report SUSPECTED ADVERSE REACTIONS, contact Validus Pharmaceuticals LLC at 1-866-982-5438 or FDA at 1-800-FDA-1088 or www.fda.gov/medwatch.

OVERDOSAGE

Overdosage can lead to acute profound water loss, volume and electrolyte depletion, dehydration, reduction of blood volume and circulatory collapse with a possibility of vascular thrombosis and embolism. Electrolyte depletion may be manifested by weakness, dizziness, mental confusion, anorexia, lethargy, vomiting and cramps. Treatment consists of replacement of fluid and electrolyte losses by careful monitoring of the urine and electrolyte output and serum electrolyte levels.

DOSAGE AND ADMINISTRATION

Individualize dosage with careful monitoring of patient response.

Oral Administration

The usual total daily dosage of Bumex tablets is 0.5 mg to 2 mg and in most patients is given as a single dose.

If the diuretic response to an initial dose of Bumex tablets is not adequate, in view of its rapid onset and short duration of action, a second or third dose may be given at 4- to 5-hour intervals up to a maximum daily dose of 10 mg. An intermittent dose schedule, whereby Bumex tablets are given on alternate days or for 3 to 4 days with rest periods of 1 to 2 days in between, is recommended as the safest and most effective method for the continued control of edema. In patients with hepatic failure, keep the dosage to a minimum.

Because cross-sensitivity with furosemide has rarely been observed, bumetanide can be substituted at approximately a 1:40 ratio of bumetanide in proportion to furosemide in patients allergic to furosemide.

Parenteral Administration

Bumetanide injection may be administered parenterally (intravenously and intramuscularly) to patients in whom gastrointestinal absorption may be impaired or in whom oral administration is not practical.

Terminate parenteral treatment and institute oral treatment as soon as possible.

HOW SUPPLIED

Bumex Tablets for oral administration are elliptical, flat-faced, and bevel-edged, available as:

Dosage | Color | Engraving | NDC 30698-xxx-xx
 |  |  | Bottle of 100 | Bottle of 500
0.5 mg | Light Green | BUMEX 0.5 | 630-01 | —
1 mg | Yellow | BUMEX 1 | 631-01 | 631-05
2 mg | Peach | BUMEX 2 | 632-01 | 632-05

Store at 68° to 77°F (20° to 25°C); excursions permitted between 59° to 86°F (15° to 30°C) [See USP Controlled Room Temperature].

Dispense contents in a tight, light-resistant container as defined in the USP with a child-resistant closure, as required.

Manufactured for and Distributed by:
Validus Pharmaceuticals LLC
Parsippany, NJ 07054
info@validuspharma.com
www.validuspharma.com
1-866-982-5438

Product of Italy

© 2023 Validus Pharmaceuticals LLC

60018-05 November 2023

PRINCIPAL DISPLAY PANEL

NDC 30698-630-01
Bumex®
(bumetanide) Tablets
0.5 mg
100 Tablets
Rx Only

PRINCIPAL DISPLAY PANEL

NDC 30698-631-01
Bumex®
(bumetanide) Tablets
1 mg
100 Tablets
Rx Only

NDC 30698-631-05
Bumex®
(bumetanide) Tablets
1 mg
500 Tablets
Rx Only

PRINCIPAL DISPLAY PANEL

NDC 30698-632-01
Bumex®
(bumetanide) Tablets
2 mg
100 Tablets
Rx Only

NDC 30698-632-05
Bumex®
(bumetanide) Tablets
2 mg
500 Tablets
Rx Only